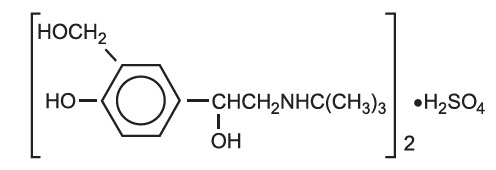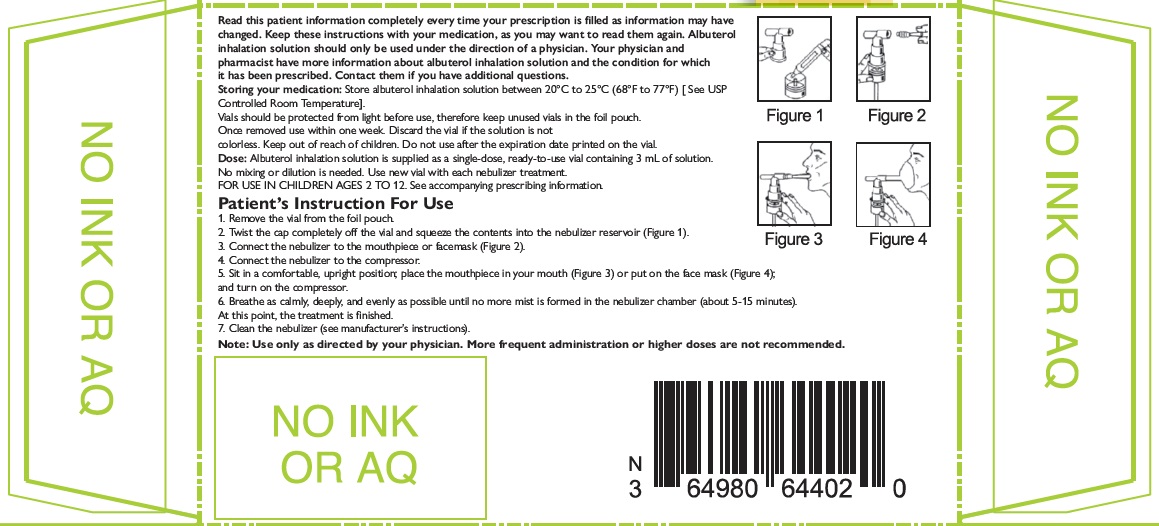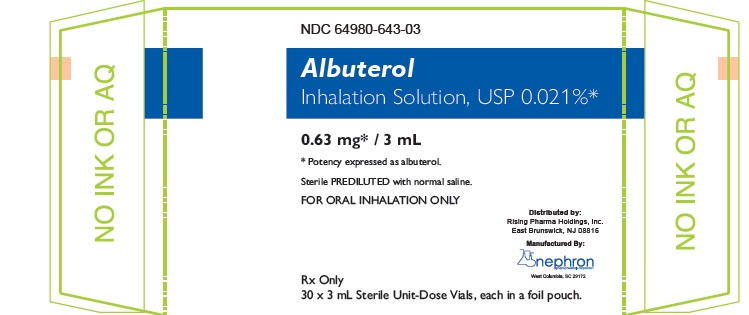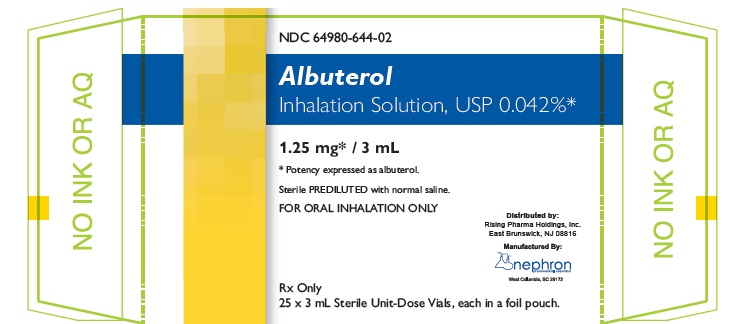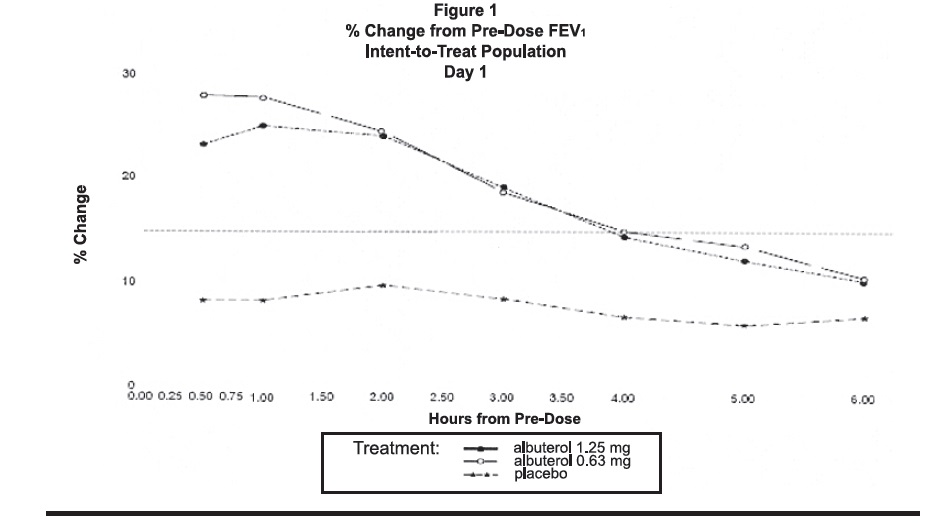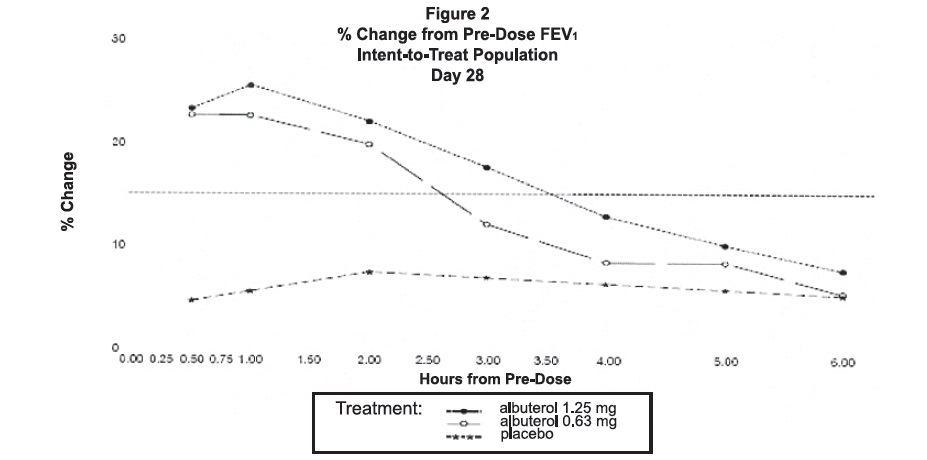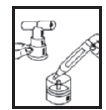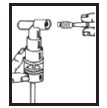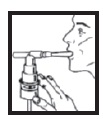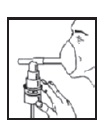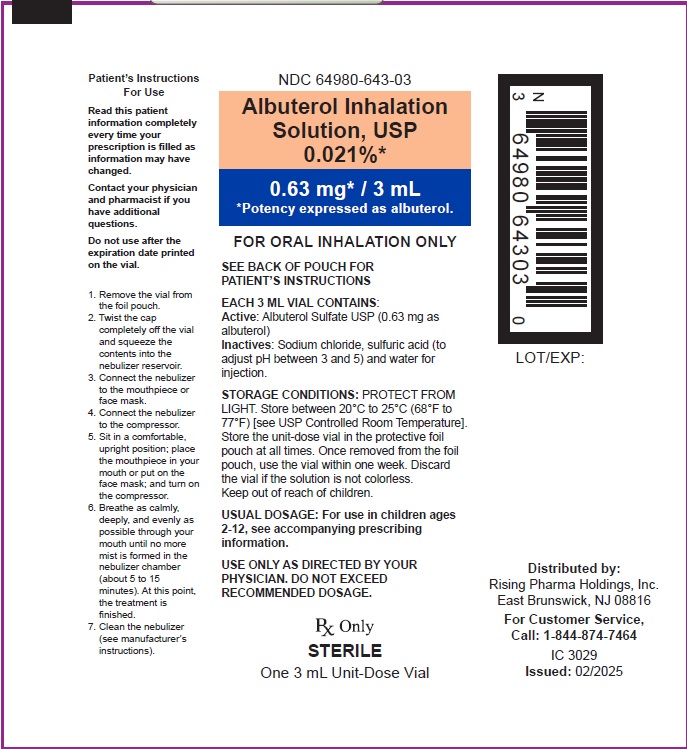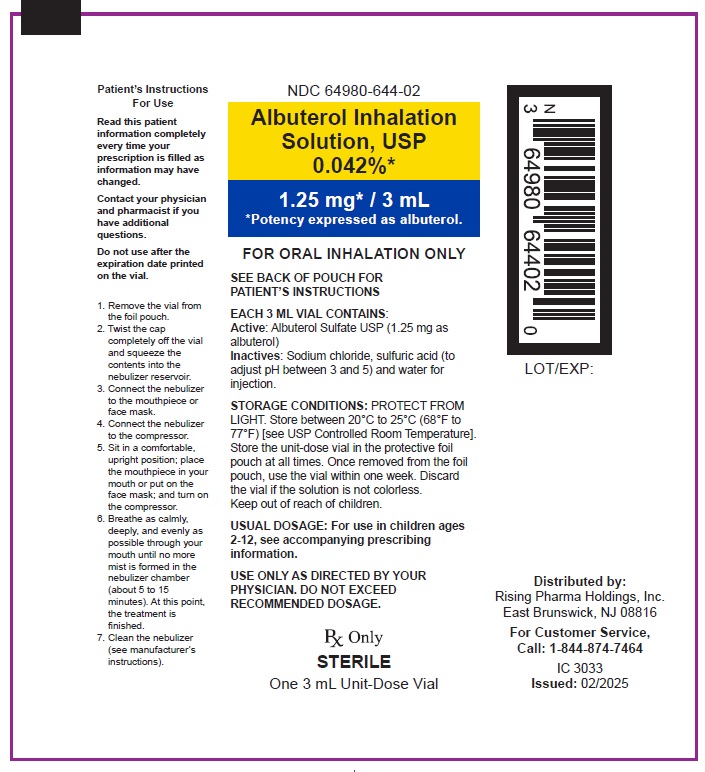 DRUG LABEL: Albuterol Sulfate
NDC: 64980-644 | Form: SOLUTION
Manufacturer: Rising Pharma Holdings, Inc
Category: prescription | Type: HUMAN PRESCRIPTION DRUG LABEL
Date: 20250417

ACTIVE INGREDIENTS: ALBUTEROL SULFATE 1.25 mg/3 mL
INACTIVE INGREDIENTS: WATER; SODIUM CHLORIDE; SULFURIC ACID

Albuterol Inhalation Solution, USP 0.021% * (0.63 mg* / 3 mL) and 0.042%* (1.25 mg* / 3 mL)

*Potency expressed as albuterol

PRESCRIBING INFORMATION

FOR INHALATION USE ONLY – NOT FOR INJECTION.

DESCRIPTION

Albuterol inhalation solution, USP is a sterile, clear, colorless solution of the sulfate salt of racemic albuterol, albuterol sulfate USP. Albuterol sulfate USP is a relatively selective beta2-adrenergic bronchodilator (see CLINICAL PHARMACOLOGY). The chemical name for albuterol sulfate is α1-[(tert-Butylamino)methyl]-4-hydroxy- m-xylene-α,α'-diol sulfate (2:1) (salt), and its established chemical structure is as follows:

The molecular weight of albuterol sulfate USP is 576.7 and the empirical formula is (C13H21NO3)2 • H2SO4. Albuterol sulfate, USP is a white crystalline powder, soluble in water and slightly soluble in ethanol. The World Health Organization’s recommended name for albuterol is salbutamol.

Albuterol inhalation solution, USP is supplied in two strengths in unit-dose vials. Each unit-dose vial contains either 0.75 mg of albuterol sulfate USP (equivalent to 0.021% or 0.63 mg of albuterol) or 1.5 mg of albuterol sulfate USP (equivalent to 0.042% or 1.25 mg of albuterol) with sodium chloride and sulfuric acid in a 3 mL isotonic, sterile, aqueous solution. Sodium chloride is added to adjust isotonicity of the solution and sulfuric acid is added to adjust pH of the solution to between 3 and 5 (see HOW SUPPLIED).

Albuterol inhalation solution, USP does not require dilution prior to administration by nebulization. For albuterol inhalation solution, USP like all other nebulized treatments, the amount delivered to the lungs will depend on patient factors, the jet nebulizer utilized, and compressor performance. Using the Pari LC Plus™ nebulizer (with face mask or mouthpiece) connected to a Pari PRONEB™ compressor, under in vitroconditions, the mean delivered dose from the mouth piece (% nominal dose) was approximately 43% of albuterol (0.042% or 1.25 mg strength) and 39% of albuterol (0.021% or 0.63 mg strength) at a mean flow rate of 3.6 L/min. The mean nebulization time was 15 minutes or less.

Albuterol inhalation solution, USP should be administered from a jet nebulizer at an adequate flow rate, via a mouthpiece or face mask (see DOSAGE AND ADMINISTRATION).

CLINICAL PHARMACOLOGY

The prime action of beta-adrenergic drugs is to stimulate adenyl cyclase, the enzyme which catalyzes the formation of cyclic-3',-5'-adenosine monophosphate (cyclic AMP) from adenosine triphosphate (ATP). The cyclic AMP thus formed mediates the cellular responses. In vitrostudies and in vivopharmacologic studies have demonstrated that albuterol has a preferential effect on beta2-adrenergic receptors compared with isoproterenol. While it is recognized that beta2-adrenergic receptors are the predominant receptors in bronchial smooth muscle, recent data indicate that 10% to 50% of the beta-receptors in the human heart may be beta2-receptors. The precise function of these receptors, however, is not yet established. Controlled clinical studies and other clinical experience have shown that inhaled albuterol, like other beta-adrenergic agonist drugs, can produce a significant cardiovascular effect in some patients, as measured by pulse rate, blood pressure, symptoms, and/or electrocardiographic changes. Albuterol is longer acting than isoproterenol in most patients by any route of administration because it is not a substrate for the cellular uptake processes for catecholamines nor for catechol- O-methyl transferase.

PHARMACOKINETICS

Pharmacokinetics:Studies in asthmatic patients have shown that less than 20% of a single albuterol dose was absorbed following either intermittent positive-pressure breathing (IPPB) or nebulizer administration; the remaining amount was recovered from the nebulizer and apparatus, and expired air. Most of the absorbed dose was recovered in urine collected during the 24 hours after drug administration.

Following oral administration of 4 mg albuterol, the elimination half-life was five to six hours. Following a 3 mg dose of nebulized albuterol in adults, the mean maximum albuterol plasma level at 0.5 hours was 2.1 ng/mL (range, 1.4 to 3.2 ng/mL). The pharmacokinetics of albuterol following administration of 0.63 mg (0.021%) or 1.25 mg (0.042%) albuterol inhalation solution by nebulization have not been determined in children 2 to 12 years old.

ANIMAL PHARMACOLOGY AND OR TOXICOLOGY

Animal Pharmacology/ Toxicology:Intravenous studies in rats with albuterol sulfate have demonstrated that albuterol crosses the blood-brain barrier and reaches brain concentrations amounting to approximately 5% of plasma concentrations. In structures outside the blood-brain barrier (pineal and pituitary glands), albuterol concentrations were found to be 100 times those found in whole brain.

Studies in laboratory animals (minipigs, rodents, and dogs) have demonstrated the occurrence of cardiac arrhythmias and sudden death (with histologic evidence of myocardial necrosis) when beta-agonists and methylxanthines are administered concurrently. The clinical significance of these findings is unknown.

CLINICAL STUDIES

Clinical Trials:The safety and efficacy of albuterol inhalation solution was evaluated in a 4-week, multi-center, randomized, double-blind, placebo-controlled, parallel group study in 349 children 6 to 12 years of age with mild-to-moderate asthma (mean baseline FEV160% to 70% of predicted). Approximately half of the patients were also receiving inhaled corticosteroids. Patients were randomized to receive albuterol inhalation solution 0.63 mg (0.021%), albuterol inhalation solution 1.25 mg (0.042%), or placebo three times a day administered via a Pari LC Plus™ nebulizer and a Pari PRONEB™ compressor. Racemic albuterol, delivered by a chlorofluorocarbon (CFC) metered dose inhaler (MDI) or nebulized, was used on an as-needed basis as the rescue medication.

Efficacy, as measured by the mean percent change from baseline in the area under the 6-hour curve for FEV1, was demonstrated for both active treatment regimens (n=112 [1.25 mg or 0.042% group] and n=110 [0.63 mg or 0.021% group]) compared with placebo (n=110) on day 1 and day 28. Figures 1 and 2 illustrate the mean percentage change from pre-dose FEV1on day 1 and day 28, respectively. The mean baseline FEV1for all patients was 1.49 L.

The onset of a 15% increase in FEV1over baseline for both doses of albuterol inhalation solution was seen at 30 minutes (the first post-dose assessment). The mean time to peak effect was approximately 30 to 60 minutes for both doses on day 1 and after 4 weeks of treatment.

The mean duration of effect, as measured by a >15% increase from baseline in FEV1, was approximately 2.5 hours for both doses on day 1 and approximately 2 hours for both doses after 4 weeks of treatment. In some patients, the duration of effect was as long as 6 hours.

INDICATIONS AND USAGE

Albuterol inhalation solution is indicated for the relief of bronchospasm in patients 2 to 12 years of age with asthma (reversible obstructive airway disease).

CONTRAINDICATIONS

Albuterol inhalation solution is contraindicated in patients with a history of hypersensitivity to any of its components.

WARNINGS

Paradoxical Bronchospasm:As with other inhaled beta-adrenergic agonists, albuterol inhalation solution can produce paradoxical bronchospasm, which may be life-threatening. If paradoxical bronchospasm occurs, albuterol inhalation solution should be discontinued immediately and alternative therapy instituted. It should be noted that paradoxical bronchospasm, when associated with inhaled formulations, frequently occurs with the first use of a new canister or vial.

Use of Anti-Inflammatory Agents:The use of beta-adrenergic bronchodilators alone may not be adequate to control asthma in many patients. Early consideration should be given to adding anti-inflammatory agents (e.g., corticosteroids).

Deterioration of Asthma:Asthma may deteriorate acutely over a period of hours or chronically over several days or longer. If the patient needs more doses of albuterol inhalation solution than usual, this may be a marker of destabilization of asthma and requires reevaluation of the patient and the treatment regimen, giving special consideration of the possible need for anti-inflammatory treatment (e.g., corticosteroids).

Fatalities have been reported in association with excessive use of inhaled sympathomimetic drugs and with the home use of nebulizers. It is, therefore, essential that the physician instruct the patient in the need for further evaluation, if his/her asthma becomes worse.

Cardiovascular Effects:Albuterol inhalation solution, like other beta-adrenergic agonists, can produce a clinically significant cardiovascular effect in some patients as measured by pulse rate, blood pressure, and/or symptoms. Although such effects are uncommon for albuterol inhalation solution at recommended doses, if they occur, the drug may need to be discontinued. In addition, beta-agonists have been reported to produce ECG changes, such as flattening of the T-wave, prolongation of the QTc interval, and ST segment depression. The clinical significance of these findings is unknown. Therefore, albuterol inhalation solution, like all other sympathomimetic amines, should be used with caution in patients with cardiovascular disorders, especially coronary insufficiency, cardiac arrhythmias, and hypertension.

Immediate Hypersentivity Reactions:Immediate hypersensitivity reactions may occur after administration of albuterol as demonstrated by rare cases of urticaria, angioedema, rash, bronchospasm, and oropharyngeal edema.

PRECAUTIONS

GENERAL PRECAUTIONS

General:Large doses of intravenous albuterol have been reported to aggravate pre-existing diabetes mellitus and ketoacidosis. As with other beta-agonists, inhaled and intravenous albuterol may produce a significant hypokalemia in some patients, possibly through intracellular shunting, which has the potential to produce adverse cardiovascular effects. The decrease is usually transient, not requiring potassium supplementation.

PATIENT COUNSELING INFORMATION

Information for Patients:The action of albuterol inhalation solution may last up to six hours, and therefore it should not be used more frequently than recommended. Do not increase the dose or frequency of medication without consulting your physician.

If you find that treatment with albuterol inhalation solution becomes less effective for symptomatic relief, your symptoms become worse, and/or you need to use the product more frequently than usual, you should seek medical attention immediately. All asthma medication should only be used under the supervision and direction of a physician. Common effects with medications such as albuterol inhalation solution include palpitations, chest pain, rapid heart rate, tremor, or nervousness.

If you are pregnant or nursing, contact your physician about the use of albuterol inhalation solution. Effective and safe use of albuterol inhalation solution includes an understanding of the way it should be administered.

If the solution in the vial changes color or becomes cloudy, you should not use it. The drug compatibility (physical and chemical), clinical efficacy, and safety of albuterol inhalation solution, when mixed with other drugs in a nebulizer, have not been established.

See illustrated Patient’s Instructions for Use

DRUG INTERACTIONS

Drug Interactions:Other short-acting sympathomimetic aerosol bronchodilators or epinephrine should not be used concomitantly with albuterol inhalation solution. Albuterol inhalation solution should be administered with extreme caution to patients being treated with monoamine oxidase inhibitors or tricyclic antidepressants or within 2 weeks of discontinuation of such agents, since the action of albuterol on the vascular system may be potentiated.

Beta-receptor blocking agents not only block the pulmonary effect of beta-agonists, such as albuterol inhalation solution, but may produce severe bronchospasm in asthmatic patients. Therefore, patients with asthma should not normally be treated with beta-blockers. However, under certain circumstances (e.g., prophylaxis after myocardial infarction), there may be no acceptable alternatives to the use of beta-adrenergic blocking agents in patients with asthma. In this setting, cardioselective beta-blockers should be considered, although they should be administered with caution. The ECG changes and/or hypokalemia that may result from the administration of non-potassium sparing diuretics (such as loop or thiazide diuretics) can be acutely worsened by beta-agonists, especially when the dose of the beta-agonist is exceeded. Although the clinical significance of these effects is unknown, caution is advised in the co-administration of beta-agonists with non-potassium sparing diuretics. Mean decreases of 16% to 22% in serum digoxin levels were demonstrated after single dose intravenous and oral administration of albuterol, respectively, to normal volunteers who had received digoxin for 10 days. The clinical significance of these findings for patients with obstructive airway disease who are receiving albuterol and digoxin on a chronic basis is unclear. Nevertheless, it would be prudent to carefully evaluate the serum digoxin levels in patients who are currently receiving digoxin and albuterol.

CARCINOGENESIS AND MUTAGENESIS AND IMPAIRMENT OF FERTILITY

Carcinogenesis, Mutagenesis, Impairment of Fertility:In a 2-year study in Sprague-Dawley rats, albuterol sulfate caused a significant dose-related increase in the incidence of benign leiomyomas of the mesovarium at and above dietary doses of 2 mg/kg (approximately equivalent to the maximum recommended daily inhalation dose for albuterol sulfate on a mg/m^2 basis). In another study, this effect was blocked by the co-administration of propranolol, a non-selective beta-adrenergic antagonist.

In an 18-month study in CD-1 mice, albuterol sulfate showed no evidence of tumorigenicity at dietary doses up to 500 mg/kg (approximately 140 times the maximum recommended daily inhalation dose of albuterol sulfate on a mg/m^2 basis). In a 22-month study in Golden hamsters, albuterol sulfate showed no evidence of tumorigenicity at dietary doses up to 50 mg/kg (approximately 20 times the maximum recommended daily inhalation dose of albuterol sulfate on a mg/m^2 basis). Albuterol sulfate was not mutagenic in the Ames test or a mutation test in yeast. Albuterol sulfate was not clastogenic in a human peripheral lymphocyte assay or in an AH1strain mouse micronucleus assay.

Reproduction studies in rats demonstrated no evidence of impaired fertility at oral doses of albuterol sulfate up to 50 mg/kg (approximately 30 times the maximum recommended daily inhalation dose of albuterol sulfate on a mg/m^2 basis).

PREGNANCY

TERATOGENIC EFFECTS

TERATOGENIC EFFECTS

Pregnancy: Teratogenic Effects: Pregnancy Category C:Albuterol has been shown to be teratogenic in mice. A study in CD-1 mice given albuterol subcutaneously showed cleft palate formation in 5 of 111 (4.5%) fetuses at 0.25 mg/kg (less than the maximum recommended daily inhalation dose of albuterol sulfate on a mg/m^2 basis) and cleft palate formation in 10 of 108 (9.3%) fetuses at 2.5 mg/kg (approximately equal to the maximum recommended daily inhalation dose of albuterol sulfate on a mg/m^2 basis). The drug did not induce cleft palate formation when administered subcutaneously at a dose of 0.025 mg/kg (less than the maximum recommended daily inhalation dose of albuterol sulfate on a mg/m^2 basis). Cleft palate formation also occurred in 23 of 72 (30.5%) fetuses from females treated subcutaneously with 2.5 mg/kg isoproterenol (positive control). A reproduction study in Stride rabbits revealed cranioschisis in 7 of 19 (37%) fetuses when albuterol sulfate was administered orally at 50 mg/kg (approximately 60 times the maximum recommended daily inhalation dose of albuterol sulfate on a mg/m^2 basis). A study in which pregnant rats were dosed with radiolabelled albuterol sulfate demonstrated that drug-related material was transferred from the maternal circulation to the fetus.

There are no adequate and well-controlled studies of the use of albuterol sulfate in pregnant women. Albuterol should be used during pregnancy only if the potential benefit justifies the potential risk to the fetus. During worldwide marketing experience, various congenital anomalies, including cleft palate and limb defects, have been reported in the offspring of patients being treated with albuterol. Some of the mothers were taking multiple medications during their pregnancies. Because no consistent pattern of defects can be discerned, a relationship between albuterol use and congenital anomalies has not been established.

Labor and Delivery:Oral albuterol has been shown to delay pre-term labor in some reports. There are presently no well-controlled studies that demonstrate that it will stop pre-term labor or prevent labor at term. Because of the potential for beta-agonist interference with uterine contractility, use of albuterol inhalation solution for relief of bronchospasm during labor should be restricted to those patients in whom the benefits clearly outweigh the risk. Albuterol has not been approved for the management of pre-term labor. The benefit:risk ratio when albuterol is administered for tocolysis has not been established. Serious adverse reactions, including pulmonary edema, have been reported following administration of albuterol to women in labor.

NURSING MOTHERS

Nurisng Mothers:It is not known whether this drug is excreted in human milk. Because of the potential for tumorigenicity shown for albuterol in some animal studies, a decision should be made whether to discontinue nursing or to discontinue the drug, taking into account the importance of the drug to the mother.

PEDIATRIC USE

Pediatric Use:Safety and effectiveness of albuterol inhalation solution 1.25 mg (0.042%) and 0.63 mg (0.021%) have been established in pediatric patients between the ages of 2 and 12 years. The use of albuterol inhalation solution in these age groups is supported by evidence from adequate and well-controlled studies of albuterol inhalation solution in children age 6 to 12 years and published reports of albuterol sulfate trials in pediatric patients 3 years of age and older. The safety and effectiveness of albuterol inhalation solution in children below 2 years of age have not been established.

ADVERSE REACTIONS

Clinical Trial Experience:Adverse events reported in >1% of patients receiving albuterol sulfate and more frequently than in patients receiving placebo in a four-week double-blind study are listed in the following table 1.

Table 1: Adverse Events with an Incidence of >1% of Patients Receiving Albuterol Inhalation Solution and Greater than Placebo (expressed as % of treatment group)
 | 1.25 mg (0.042%) Albuterol Inhalation Solution (n = 115) | 0.63 mg (0.021%) Albuterol Inhalation Solution (n = 117) | Placebo (n = 117)
Asthma Exacerbation | 13 | 11.1 | 8.5
Otitis Media | 4.3 | 0.9 | 0
Allergic Reaction | 0.9 | 3.4 | 1.7
Gastroenteritis | 0.9 | 3.4 | 0.9
Cold Symptoms | 0 | 3.4 | 1.7
Flu Syndrome | 2.6 | 2.6 | 1.7
Lymphadenopathy | 2.6 | 0.9 | 1.7
Skin/Appendage Infection | 1.7 | 0 | 0
Urticaria | 1.7 | 0.9 | 0
Migraine | 0.9 | 1.7 | 0
Chest Pain | 0.9 | 1.7 | 0
Bronchitis | 0.9 | 1.7 | 0.9
Nausea | 1.7 | 0.9 | 0.9

There was one case of ST segment depression in the 1.25 mg (0.042%) albuterol inhalation solution treatment group.

No clinically relevant laboratory abnormalities related to albuterol inhalation solution administration were seen in this study.

Postmarketing Experience:Metabolic acidosis has been reported after the use of albuterol inhalation solution. Because this reaction is reported voluntarily from a population of uncertain size, it is not always possible to reliably estimate its frequency or establish a causal relationship to drug exposure.

OVERDOSAGE

The expected symptoms with overdosage are those of excessive beta-adrenergic stimulation and/or occurrence or exaggeration of symptoms such as seizures, angina, hypertension or hypotension, tachycardia with rates up to 200 beats per minute, arrhythmias, nervousness, headache, tremor, dry mouth, palpitation, nausea, dizziness, fatigue, malaise, insomnia, and exaggeration of the pharmacological effects listed in ADVERSE REACTIONS. Hypokalemia may also occur. As with all sympathomimetic aerosol medications, cardiac arrest and even death may be associated with abuse of albuterol inhalation solution. Treatment consists of discontinuation of albuterol inhalation solution together with appropriate symptomatic therapy. The judicious use of a cardioselective beta-receptor blocker may be considered, bearing in mind that such medication can produce bronchospasm. There is insufficient evidence to determine if dialysis is beneficial for overdosage of albuterol inhalation solution. The oral median lethal dose of albuterol sulfate in mice is greater than 2000 mg/kg (approximately 580 times the maximum recommended daily inhalation dose of albuterol sulfate on a mg/m^2 basis). The subcutaneous median lethal dose of albuterol sulfate in mature rats and small young rats is approximately 450 mg/kg and 2000 mg/kg, respectively (approximately 260 and 1200 times the maximum recommended daily inhalation dose of albuterol sulfate on a mg/m^2 basis). The inhalation median lethal dose has not been determined in animals.

HOW SUPPLIED

Albuterol inhalation solution, USP is supplied as a 3 mL, clear, colorless, sterile, preservative-free, aqueous solution in two different strengths, 0.63 mg (0.021%) of albuterol (equivalent to 0.75 mg of albuterol sulfate in 3 mL) and 1.25 mg (0.042%) of albuterol (equivalent to 1.5 mg of albuterol sulfate in 3 mL) in unit-dose low-density polyethylene (LDPE) vials. Each unit-dose LDPE vial is protected in a foil pouch, and each foil pouch contains 1 unit-dose LDPE vial.Each strength of albuterol inhalation solution is available in a shelf carton containing multiple foil pouches.

Albuterol inhalation solution, USP 0.021%* (0.63 mg* / 3 mL)(*potency expressed as albuterol) in unit-dose vials and is available in the following packaging configurations:

NDC 64980-643-03 30 foil pouches, each containing 1 vial, total 30 vials per carton

Albuterol inhalation solution, USP 0.042%* (1.25 mg* / 3 mL)(potency expressed as albuterol) in unit-dose vials and is available in the following packaging configurations:

NDC 64980-644-02 25 foil pouches, each containing 1 vial, total 25 vials per carton

NDC 64980-644-03 30 foil pouches, each containing 1 vial, total 30 vials per carton

STORAGE:

Store between 20°C to 25°C (68°F to 77°F), excursions permitted to 15°C to 30°C (59°F to 86°F) [see USP Controlled Room Temperature]. Protect from light and excessive heat. Store unit-dose vials in protective foil pouch at all times.

Once removed from the foil pouch, use vial within one week. Discard the vial if the solution is not colorless.

Keep out of the reach of children.

Rx Only

Distributed by:

Rising Pharma Holdings, Inc.

East Brunswick, NJ 08816

For Customer Service,

Call: 1-844-874-7464

Issued:02/2025

IC 3032

Manufactured By:
Nephron Pharmaceuticals Corporation
West Columbia, SC 29172

DOSAGE AND ADMINISTRATION

The usual starting dosage for patients 2 to 12 years of age is 1.25 mg (0.042%) or 0.63 mg (0.021%) of albuterol inhalation solution administered 3 or 4 times daily, as needed, by nebulization. More frequent administration is not recommended. To administer 1.25 mg or 0.63 mg of albuterol, use the entire contents of one unit-dose vial (3 mL of 0.042% [1.25 mg] or 3 mL of 0.021% [0.63 mg] inhalation solution) by nebulization. Adjust nebulizer flow rate to deliver albuterol inhalation solution over 5 to 15 minutes. The use of albuterol inhalation solution can be continued as medically indicated to control recurring bouts of bronchospasm. During this time most patients gain optimum benefit from regular use of the inhalation solution. Patients 6 to 12 years of age with more severe asthma (baseline FEV1less than 60% predicted), weight > 40 kg, or patients 11 to 12 years of age may achieve a better initial response with the 1.25 mg dose. albuterol inhalation solution has not been studied in the setting of acute attacks of bronchospasm. A 2.5 mg dose of albuterol provided by a higher concentration product (2.5 mg albuterol per 3 mL) may be more appropriate for treating acute exacerbations, particularly in children 6 years old and above. If a previously effective dosage regimen fails to provide the usual relief, medical advice should be sought immediately, as this is often a sign of seriously worsening asthma which would require reassessment of therapy. The drug compatibility (physical and chemical), clinical efficacy and safety of albuterol inhalation solution, when mixed with other drugs in a nebulizer have not been established. The safety and efficacy of albuterol inhalation solution have been established in clinical trials when administered using the Pari LC Plus™ nebulizer and Pari PRONEB™ compressor. The safety and efficacy of albuterol inhalation solution when administered with other nebulizer systems have not been established. Albuterol inhalation solution should be administered via jet nebulizer connected to an air compressor with adequate air flow, equipped with a mouthpiece or suitable face mask.

Patient Package Insert

Read this patient information completely every time your prescription is filled as information may have changed. Keep these instructions with your medication, as you may want to read them again. Albuterol inhalation solution should only be used under the direction of a physician. Your physician and pharmacist have more information about albuterol inhalation solution and the condition for which it has been prescribed. Contact them if you have additional questions.

Storing your medication:Store albuterol inhalation solution between 20°C to 25°C (68°F to 77°F). [See USP Controlled Room Temperature].

Vials should be protected from light before use, therefore keep unused vials in the foil pouch.

Once removed use within one week. Discard the vial if the solution is not colorless.

Keep out of reach of children. Do not use after the expiration date printed on the vial.

Dose:Albuterol inhalation solution is supplied as a single-dose, ready-to-use vial containing 3 mL of solution. No mixing or dilution is needed. Use new vial with each nebulizer treatment.

FOR USE IN CHILDREN AGES 2 TO 12. See accompanying prescribing information.

Patient's Instruction For Use

1. Remove one vial from the foil pouch.
2. Twist the cap completely off the vial and squeeze the contents into the nebulizer reservoir (Figure 1).

3. Connect the nebulizer to the mouthpiece or face mask (Figure 2).

4. Connect the nebulizer to the compressor.

5. Sit in a comfortable, upright position; place the mouthpiece in your mouth (Figure 3) or put on the face mask (Figure 4); and turn on the compressor.

6. Breathe as calmly, deeply, and evenly as possible until no more mist is formed in the nebulizer chamber (about 5-15 minutes). At this point, the treatment is finished.

7.Clean the nebulizer (see manufacturer's instructions).

Note: Use only as directed by your physcian. More frequent administration or higher doses are not recommended.

PATIENT INFORMATION

Albuterol Inhalation Solution, USP

0.021%* (0.63 mg* / 3 mL) and 0.042%* (1.25mg* / 3mL)

*Potency expressed as albuterol

Prescription Only.

Read the patient information that comes with albuterol inhalation solution before using it and each time you get a refill for your child. There may be new information. This leaflet does not take the place of talking to your child’s doctor about your child’s medical condition or treatment.

What is albuterol inhalation solution?

Albuterol inhalation solution is a medicine that is used for the relief of bronchospasms caused by asthma in children ages 2 to 12 years. Bronchospasm is the tightening and swelling of the muscles around the airways. Albuterol inhalation solution can help relax these airway muscles for up to 6 hours so that your child may breathe more easily.

Who should not use albuterol inhalation solution?

Do not give your child albuterol inhalation solution if he or she is allergic to any of its ingredients. The active ingredient is albuterol sulfate. See the end of this leaflet for a complete list of ingredients.

What should I tell my child’s doctor before giving albuterol inhalation solution?

Tell your child’s doctor about all of your child’s medical conditions including if your child has:

- Heart problems
- High blood pressure
- Seizures
- A thyroid problem called hyperthyroidism
- Diabetes

Tell your child’s doctor about all the medicines your child takes, including prescription and non-prescription medicines, vitamins and herbal supplements. Albuterol inhalation solution and some other medicines can affect each other and may cause serious side effects. Especially tell your child’s doctor if your child is taking or using:

- Any short-acting bronchodilator medicines (sometimes called rescue inhalers)
- Epinephrine
- Medicines called monoamine oxidase inhibitors (MAOIs) or tricyclic antidepressants or has stopped taking them in the past 2 weeks. These medicines are usually used for mental problems.
- Medicines called beta-blockers (used for heart problems and high blood pressure)
- Certain diuretic medicines (water pills)
- Digoxin

Know the medicines your child takes. Keep a list of them and show it to your child’s doctor and pharmacist each time your child gets a new medicine.

How should albuterol inhalation solution be given?

Read the Patient’s Instructions for Usethat comes with albuterol inhalation solution. Ask your pharmacist for these instructions if they are not with your medicine. Keep the instructions with albuterol inhalation solution because you may want to read them again.

- Give albuterol inhalation solution exactly as prescribed for your child. Do not change your child’s dose or how often it is used without talking to your child’s doctor first.
- Albuterol inhalation solution is breathed into the lungs. Albuterol inhalation solution is used with a special breathing machine called a nebulizer. Do not mix other medicines with albuterol inhalation solution in the nebulizer. Do not use albuterol inhalation solution that is not clear and colorless.
- Call your child’s doctor or get emergency help right away if your child’s breathing is not helped or gets worse during treatment with albuterol inhalation solution.
- Call your child’s doctor right away if your child needs to use albuterol inhalation solution more often than prescribed.
- Albuterol inhalation solution has not been studied for treating acute attacks of bronchospasm (rescue use). Your child may need a different medicine for rescue use.
- If you give your child too much albuterol inhalation solution, call your child’s doctor right away.

What are the side effects with albuterol inhalation solution?

Albuterol inhalation solution may cause the following serious side effects:

- Worsening of the tightening and swelling of the muscles around your child’s airways (bronchospasm).This side effect can be life-threatening. Call your child’s doctor or get emergency help right away if your child’s breathing is not helped or gets worse during treatment with albuterol inhalation solution.
- Serious and life-threatening allergic reactions. Symptoms of a serious allergic reaction include:
  - Hives, rash
  - Swelling of your child’s face, eyelids, lips, tongue, or throat, and trouble swallowing
  - Worsening of your child’s breathing problems such as wheezing, chest tightness or shortness of breath
  - Shock (loss of blood pressure and consciousness).

The most common side effects with albuterol inhalation solution include a fast or irregular heartbeat, chest pain, shakiness, or nervousness.

How should albuterol inhalation solution be stored?

- Store albuterol inhalation solution at room temperature, or 68°F to 77°F (20°C to 25°C) in its tightly closed container.
- Protect vials from light before use. Therefore, keep unused vial(s) in the foil pouch or carton. Once removed from the foil pouch, use vial(s) within one week.
- Do not use albuterol inhalation solution after the expiration date printed on the vial.
- Do not use albuterol inhalation solution that is not clear and colorless.
- Safely, discard albuterol inhalation solution that is out-of-date or no longer needed.
- Keep albuterol inhalation solution and all medicines out of the reach of children.

General Information about albuterol inhalation solution

Medicines are sometimes prescribed for conditions that are not mentioned in the patient information leaflets. Do not use albuterol inhalation solution for a condition for which it was not prescribed. Do not give albuterol inhalation solution to other people, even if they have the same symptoms your child has. It may harm them.

This leaflet summarizes the most important information about albuterol inhalation solution. If you would like more information, talk with your child’s doctor. You can ask your child’s doctor or pharmacist for information about albuterol inhalation solution that is written for health professionals.

What are the ingredients in albuterol inhalation solution?

Active Ingredient:albuterol sulfate
Inactive Ingredients:sodium chloride and sulfuric acid

Rx Only

Distributed by:

Rising Pharma Holdings, Inc.

East Brunswick, NJ 08816

For Customer Service,

Call: 1-844-874-7464

Issued:02/2025

IC 3035

Manufactured By:
Nephron Pharmaceuticals Corporation
West Columbia, SC 29172

Principal Display Panel

Carton (1.25* mg)

NDC 64980-644-02

Carton (0.63mg*)

NDC 64980-643-03

Carton Back Panel (1.25* mg and 0.63*mg)

Pouch Label (1.25mg/3mL)

NDC 64980-644-02

Pouch Label (0.63mg/3mL)

NDC 64980-643-03